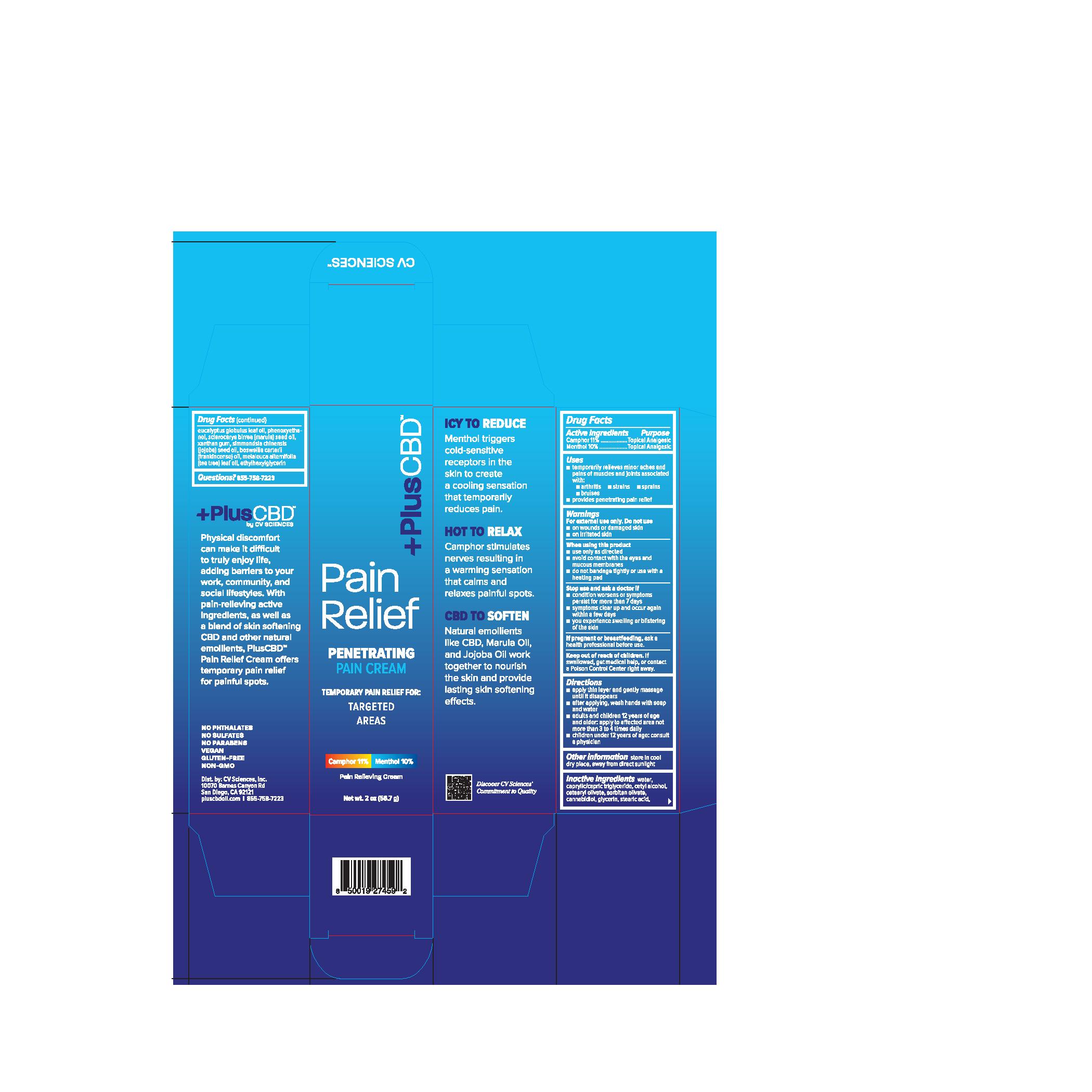 DRUG LABEL: PlusCBD Pain Cream (Penetrating) 2oz
NDC: 82026-611 | Form: CREAM
Manufacturer: CV Sciences, Inc.
Category: otc | Type: HUMAN OTC DRUG LABEL
Date: 20241211

ACTIVE INGREDIENTS: MENTHOL 10 g/100 g; CAMPHOR (NATURAL) 11 g/100 g
INACTIVE INGREDIENTS: WATER; CETEARYL OLIVATE; MEDIUM-CHAIN TRIGLYCERIDES; CETYL ALCOHOL; SORBITAN OLIVATE; CANNABIDIOL; GLYCERIN; STEARIC ACID; EUCALYPTUS OIL; PHENOXYETHANOL; SCLEROCARYA BIRREA SEED OIL; XANTHAN GUM; JOJOBA OIL; FRANKINCENSE OIL; TEA TREE OIL; ETHYLHEXYLGLYCERIN

PlusCBD Pain Cream (Penetrating) 2oz

Active ingredients

Camphor 11%

Menthol 10%

Purpose

Camphor 11%..............Topical Analgesic

Menthol 10%................Topical Analgesic

Uses

- temporarily relieves minor aches and pains of muscles and joints associated with:
- arthritis
- strains
- sprains
  - bruises
- provides penetrating pain relief

Warnings

For external use only

Do not use

- on wounds or damaged skin
- on irritated skin

When using this product

- use only as directed
- avoid contact with the eyes and mucous membranes
- do not bandage tightly or use with a heating pad

Stop use and ask a doctor if

- condition worsens or symptoms persist for more than 7 days
- symptoms clear up and occur again within a few days
- you experience swelling or blistering of the skin

PREGNANCY OR BREAST FEEDING

If pregnant or breastfeeding,ask a health professional before use.

Keep out of reach of children.If swallowed, get medical help, or contact a Poison Control Center right away.

Directions

- apply thin layer and gently massage until it disappears
- after applying, wash hands with soap and water
- adults and children 12 years of age and older: apply to affected area not more than 3 to 4 times daily
- children under 12 years of age: consult a physician

Other information

store in cool dry place, away from direct sunlight

Inactive ingredients

water, caprylic/capric triglyericde, cetyl alcohol, cetearyl olivate, sorbitan olivate, cannabidiol, glycerin, stearic acid, eucalyptus globulus leaf oil, phenoxyethanol, sclerocarya birrea (marula) seed oil, xanthan gum, simmondsia chinensis (jojoba) seed oil, boswellia carterii (frankincense) oil, melaleuca alternifolia (tea tree) leaf oil, ethylhexylglycerin

Questions?

855-758-7223

PACKAGE LABEL

+PlusCBD
Pain Relief

Penetrating Pain Cream

Temporary Pain Relief For:

Targeted Areas

Camphor 11% Menthol 10%

Pain Relieving Cream

Net wt. 2 oz (56.7 g)